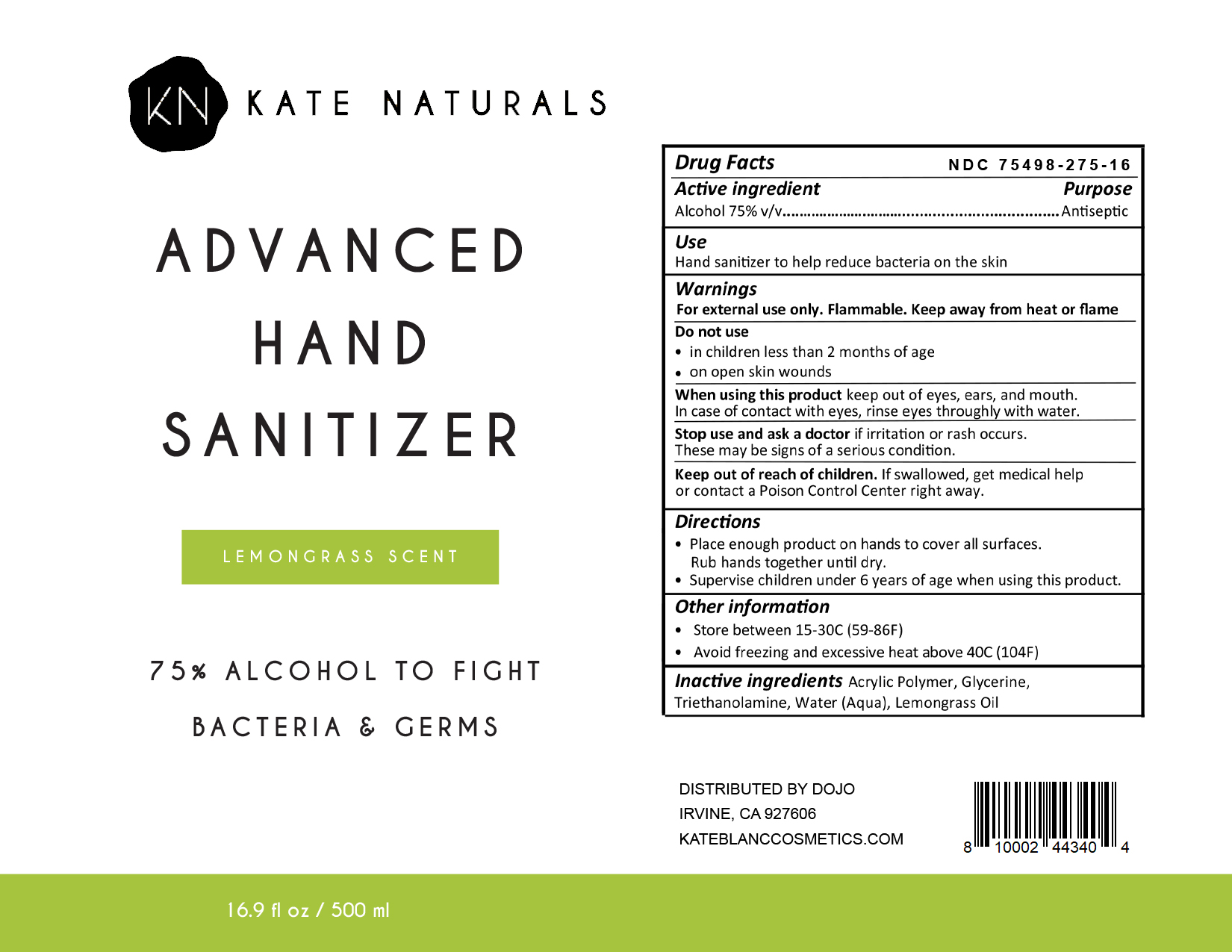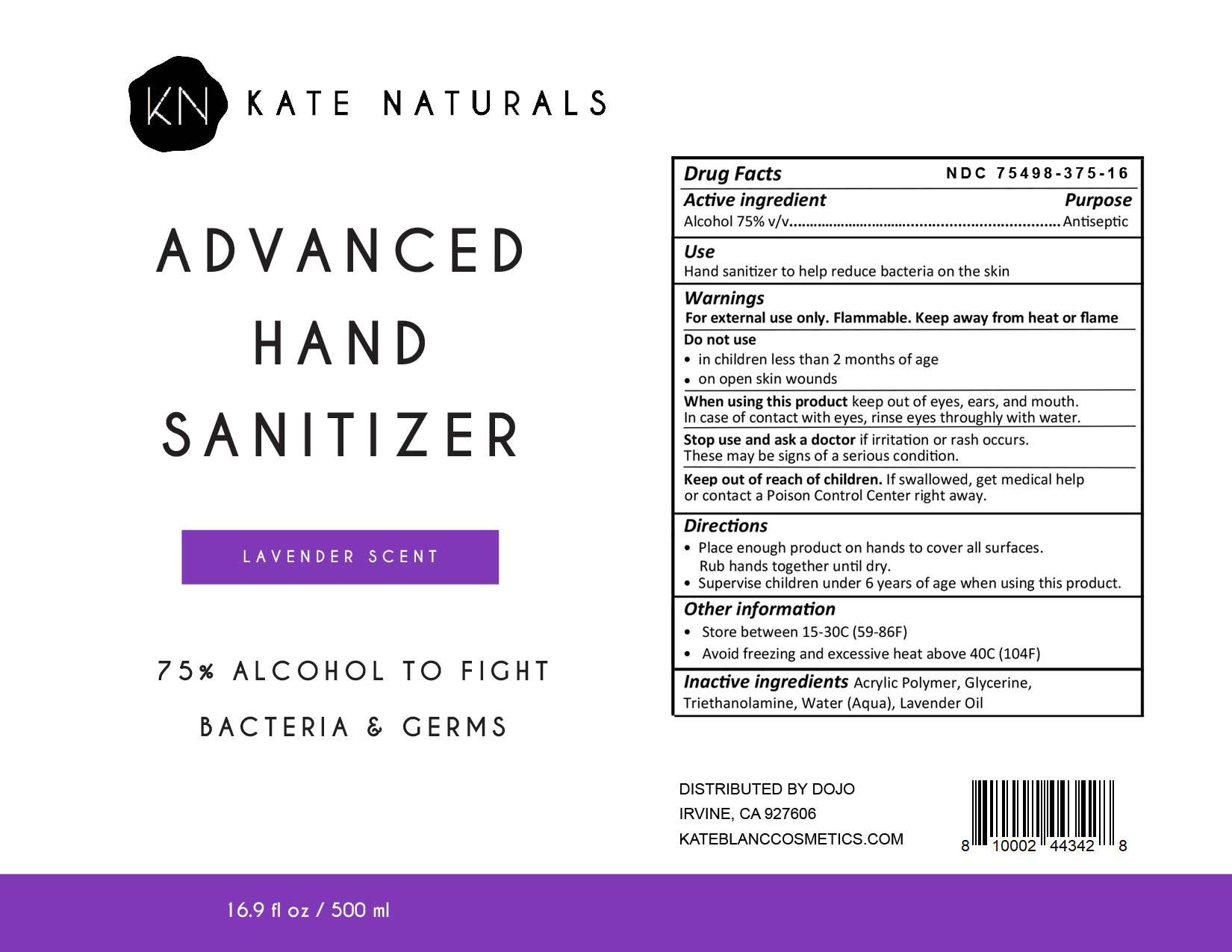 DRUG LABEL: Kate Naturals Advanced Hand Sanitizer Lemongrass Scent
NDC: 75498-275 | Form: GEL
Manufacturer: THE DOJO, LLC
Category: otc | Type: HUMAN OTC DRUG LABEL
Date: 20200612

ACTIVE INGREDIENTS: ALCOHOL 75 mL/100 mL
INACTIVE INGREDIENTS: GLYCERIN; WATER; WEST INDIAN LEMONGRASS OIL; ACRYLIC ACID/SODIUM ACRYLATE COPOLYMER (1:1; 600 MPA.S AT 0.2%); TROLAMINE

The hand sanitizer is manufactured using the following ingredients:

1. Alcohol (ethanol) (USP or Food Chemical Codex (FCC) grade) (75%, volume/volume (v/v)) in an aqueous solution denatured according to Alcohol and Tobacco Tax and Trade Bureau regulations in 27 CFR part 20.
2. Glycerine
3. Trolamine
4. Sterile distilled water or boiled cold water.
5. Acrylic Acid/Sodium Acrylate Copolymer (1:1; 600 MPA.S at 0.2%)
6. Lemongrass Oil

Active Ingredient(s)

Alcohol 75% v/v. Purpose: Antiseptic

Purpose

Antiseptic, Hand Sanitizer

Use

Hand Sanitizer to help reduce bacteria that potentially can cause disease. For use when soap and water are not available.

Warnings

For external use only. Flammable. Keep away from heat or flame

Do not use

- in children less than 2 months of age
- on open skin wounds

When using this product keep out of eyes, ears, and mouth. In case of contact with eyes, rinse eyes thoroughly with water.
Stop use and ask a doctor if irritation or rash occurs. These may be signs of a serious condition.
Keep out of reach of children. If swallowed, get medical help or contact a Poison Control Center right away.

Stop use and ask a doctor if irritation or rash persists.

Keep out of reach of children. If swallowed, get medical help or contact a Poison Control Center right away.

Directions

- Place enough product on hands to cover all surfaces. Rub hands together until dry.
- Wet hands with product thoroughly, allow to dry without wiping.
- Supervise children under 6 years of age when using this product to avoid swallowing.

Other information

- Store between 15-30C (59-86F)
- Avoid freezing and excessive heat above 40C (104F)

Inactive ingredients

glycerin, trolamine, acrylic acid/sodiu, acrylate copolymer (1:1; 600 MPA.S at 0.2%), water, lemongrass oil

Package Label - Principal Display Panel

500 mL NDC: NDC 75498-275-16

500 mL NDC: NDC 75498-375-16